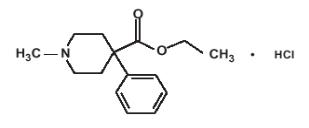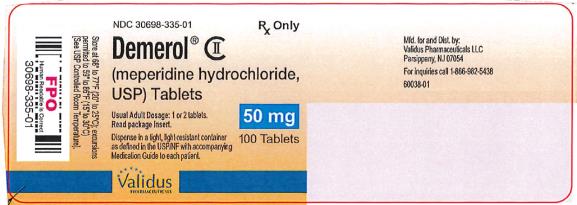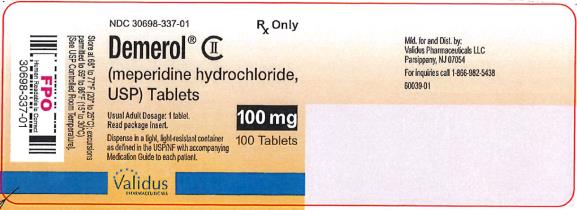 DRUG LABEL: Demerol
NDC: 30698-335 | Form: TABLET
Manufacturer: Validus Pharmaceuticals LLC
Category: prescription | Type: HUMAN PRESCRIPTION DRUG LABEL
Date: 20231225
DEA Schedule: CII

ACTIVE INGREDIENTS: MEPERIDINE HYDROCHLORIDE 50 mg/1 1
INACTIVE INGREDIENTS: CALCIUM SULFATE; CALCIUM PHOSPHATE, DIBASIC, ANHYDROUS; STARCH, CORN; STEARIC ACID; TALC

HIGHLIGHTS OF PRESCRIBING INFORMATION

These highlights do not include all the information needed to use DEMEROL® TABLETS and ORAL SOLUTION safely and effectively. See full prescribing information for DEMEROL TABLETS and ORAL SOLUTION.
DEMEROL (meperidine hydrochloride), tablets, for oral use, CII
DEMEROL (meperidine hydrochloride), oral solution CII
Initial U.S. Approval: 1942

RECENT MAJOR CHANGES

Boxed Warning | 12/2023
Indications and Usage (1) | 12/2023
Dosage and Administration (2.1, 2.3, 2.5) | 12/2023
Warning and Precautions (5.9) | 12/2023

WARNING: SERIOUS AND LIFE-THREATENING RISKS FROM USE OF DEMEROL TABLETS AND ORAL SOLUTION

See full prescribing information for complete boxed warning.

• Ensure accuracy when prescribing, dispensing, and administering DEMEROL Oral Solution. Dosing errors due to confusion between mg and mL, and other Meperidine Hydrochloride Oral Solutions of different concentrations can result in accidental overdose and death. (2.1, 5.1)

• DEMEROL Tablets and Oral Solution expose users to risks of addiction, abuse, and misuse, which can lead to overdose and death. Assess patient’s risk before prescribing and monitor regularly for these behaviors and conditions. (5.2)

• To ensure that the benefits of opioid analgesics outweigh the risks of addiction, abuse, and misuse, the Food and Drug Administration (FDA) has required a Risk Evaluation and Mitigation Strategy (REMS) for these products. (5.3)

• Serious, life-threatening, or fatal respiratory depression may occur. Monitor closely, especially upon initiation or following a dose increase. (5.4)

• Accidental ingestion of DEMEROL Tablets or Oral Solution, especially by children, can result in a fatal overdose of meperidine. (5.4)

• Prolonged use of DEMEROL Tablets or Oral Solution during pregnancy can result in neonatal opioid withdrawal syndrome, which may be life-threatening if not recognized and treated. If prolonged opioid use is required in a pregnant woman, advise the patient of the risk of neonatal opioid withdrawal syndrome and ensure that appropriate treatment will be available. (5.5)

• Concomitant use with CYP3A4 inhibitors (or discontinuation of CYP3A4 inducers) can result in fatal overdose of meperidine (5.6, 7)

• Concomitant use of opioids with benzodiazepines or other central nervous system (CNS) depressants, including alcohol, may result in profound sedation, respiratory depression, coma, and death. Reserve concomitant prescribing for use in patients for whom alternative treatment options are inadequate; limit dosages and durations to the minimum required; and follow patients for signs and symptoms of respiratory depression and sedation. (5.7, 7)

• Concomitant use of DEMEROL Tablets or Oral Solution with monoamine oxidase inhibitors (MAOIs) can result in coma, severe respiratory depression, cyanosis and hypotension. Use of DEMEROL Tablets or Oral Solution with MAOIs within the last 14 days is contraindicated. (4, 5.8, 6)

1 INDICATIONS AND USAGE

DEMEROL Tablets and Oral Solution are opioid agonists indicated for the management of pain, severe enough to require an opioid analgesic and for which alternative treatments are inadequate. (1)

Limitations of Use

Because of the risks of addiction, abuse, and misuse with opioids, which can occur at any dosage or duration, reserve DEMEROL Tablets and Oral Solution for use in patients for whom alternative treatment options (e.g., non-opioid analgesics or opioid combination products):

- Have not been tolerated, or are not expected to be tolerated (1)
- Have not provided adequate analgesia, or are not expected to provide adequate analgesia (1)

DEMEROL Tablets and Oral Solution should not be used for an extended period of time unless the pain remains severe enough to require an opioid analgesic and for which alternative treatment options continue to be inadequate.

DEMEROL Tablets and Oral Solution should not be used for the treatment of chronic pain. Use of DEMEROL Tablets and Oral Solution for an extended period of time may increase the risk of toxicity (e.g., seizures) from the accumulation of the meperidine metabolite, normeperidine.

2 DOSAGE AND ADMINISTRATION

- DEMEROL Tablets and Oral Solution should be prescribed only by healthcare professionals who are knowledgeable about the use of opioids and how to mitigate the associate risks. (2.1)
- Use the lowest effective dosage for the shortest duration of time consistent with individual patient treatment goals. Because the risk of overdose increases as opioid doses increase, reserve titration to higher doses of DEMEROL Tablets and Oral Solution for patients in whom lower doses are insufficiently effective and in whom the expected benefits of using a higher dose opioid clearly outweigh the substantial risks. (2.1, 5)
- Many acute pain conditions (e.g., the pain that occurs with a number of surgical procedures or acute musculoskeletal injuries) require no more than a few days of an opioid analgesic. Clinical guidelines on opioid prescribing for some acute pain conditions are available. (2.1)
- There is variability in the opioid analgesic dose and duration needed to adequately manage pain due both to the cause of pain and to individual patient factors. Initiate the dosing regimen for each patient individually, taking into account the patient’s underlying cause and severity of pain, prior analgesic treatment and response, and risk factors for addiction, abuse, and misuse. (2.1, 5.2)
- Respiratory depression can occur at any time during opioid therapy, especially when initiating and following dosage increases with DEMEROL Tablets and Oral Solution. Consider this risk when selecting an initial dose and when making dose adjustments. (2.1, 5.3)
- Discuss availability of naloxone with the patient and caregiver and assess each patient’s need for access to naloxone, both when initiating and renewing treatment with DEMEROL Tablets and Oral Solution. Consider prescribing naloxone based in the patient’s risk factors for overdose. (2.2, 5.2,5.4,5.7)
- Adult Patients: Initiate treatment in adults with 50 mg to 150 mg orally, every 3 to 4 hours as needed for pain, and at lowest dose necessary to achieve adequate analgesia (2.3). Titrate the dose based upon the individual patient’s response to their initial dose of DEMEROL Tablets and Oral Solution.
- Pediatric Patients: Initiate treatment in pediatric patients with 1.1 mg/kg to 1.8 mg/kg orally, up to the adult dose, every 3 or 4 hours as needed and at the lowest dose necessary to achieve adequate analgesia (2.3). Titrate the dose based upon the individual patient’s response to their initial dose of DEMEROL Tablets and Oral Solution.
- Do not abruptly discontinue DEMEROL Tablets and Oral Solution in a physically dependent patient because rapid discontinuation of opioid analgesics has resulted in serious withdrawal symptoms, uncontrolled pain, and suicide. (2.6)

3 DOSAGE FORMS AND STRENGTHS

Tablets: 50 mg and 100 mg. (3)

Oral Solution: 50mg/5mL (10 mg/mL)

4 CONTRAINDICATIONS

- Significant respiratory depression. (4)
- Acute or severe bronchial asthma in an unmonitored setting or in absence of resuscitative equipment. (4)
- Concomitant use of monoamine oxidase inhibitors (MAOIs) or within 14 days of having taken an MAOI. (4)
- Known or suspected gastrointestinal obstruction, including paralytic ileus. (4)
- Hypersensitivity to meperidine or to any other ingredients of the product. (4)

5 WARNINGS AND PRECAUTIONS

- Opioid-Induced Hyperalgesia and Allodynia: Opioid-Induced Hyperalgesia (OIH) occurs when an opioid analgesic paradoxically causes an increase in pain, or an increase in sensitivity to pain. If a patient is suspected to be experiencing OIH, carefully consider appropriately decreasing the dose of the current opioid analgesic, or opioid rotation (safety switching the patient to a different opioid moiety). (5.9)
- Serotonin Syndrome: Potentially life-threatening condition could result from concomitant serotonergic drug administration. Discontinue DEMEROL Tablets or Oral Solution if serotonin syndrome is suspected. (5.10)
- Life-Threatening Respiratory Depression in Patients with Chronic Pulmonary Disease or in Elderly, Cachectic, or Debilitated Patients: Monitor Regularly evaluate closely, particularly during initiation and titration. (5.11)
- Adrenal Insufficiency: If diagnosed, treat with physiologic replacement of corticosteroids, and wean patient off of the opioid. (5.12)
- Severe Hypotension: Regularly evaluate during dosage initiation and titration. Avoid use of DEMEROL Tablets or Oral Solution in patients with circulatory shock. (5.13)
- Risks of Use in Patients with Increased Intracranial Pressure, Brain Tumors, Head Injury, or Impaired Consciousness: Monitor for sedation and respiratory depression. Avoid use of DEMEROL Tablets or Oral Solution in patients with impaired consciousness or coma. (5.14)

6 ADVERSE REACTIONS

Most common adverse reactions were lightheadedness, dizziness, sedation, nausea, vomiting, and sweating. (6)

To report SUSPECTED ADVERSE REACTIONS, contact Validus Pharmaceuticals LLC at 1-866-982-5438 or FDA at 1-800-FDA-1088 or www.fda.gov/medwatch.

7 DRUG INTERACTIONS

- Mixed Agonist/Antagonist and Partial Agonist Opioid Analgesics: Avoid use with DEMEROL Tablets or Oral Solution because they may reduce analgesic effect of DEMEROL Tablets or Oral Solution or precipitate withdrawal symptoms. (7)

8 USE IN SPECIFIC POPULATIONS

- Pregnancy: May cause fetal harm (8.1).

FULL PRESCRIBING INFORMATION

WARNING: SERIOUS AND LIFE-THREATENING RISKS FROM USE OF DEMEROL TABLETS AND ORAL SOLUTION

Risk of Medication Errors

Ensure accuracy when prescribing, dispensing, and administering DEMEROL Oral Solution. Dosing errors due to confusion between mg and mL, and other Meperidine Hydrochloride Oral Solutions of different concentrations can result in accidental overdose and death [see Dosage and Administration (2.1), Warning and Precautions (5.1)].

Addiction, Abuse, and Misuse

Because the use of DEMEROL Tablets and Oral Solution exposes patients and other users to the risks of opioid addiction, abuse, and misuse, which can lead to overdose and death, assess each patient’s risk prior to prescribing and reassess all patients regularly for the development of these behaviors and conditions [see Warnings and Precautions (5.2)].

Life-Threatening Respiratory Depression

Serious, life-threatening, or fatal respiratory depression may occur with use of DEMEROL Tablets and Oral Solution, especially during initiation or following a dose increase. To reduce the risk of respiratory depression, proper dosing and titration of DEMEROL Tablets or Oral Solution are essential [see Warnings and Precautions (5.3)].

Accidental Ingestion

Accidental ingestion of DEMEROL Tablets and Oral Solution, especially by children, can result in a fatal overdose of meperidine [see Warnings and Precautions (5.3)].

Risk From Concomitant Use with Benzodiazepines or Other CNS Depressants

Concomitant use of opioids with benzodiazepines or other central nervous system (CNS) depressants, including alcohol, may result in profound sedation, respiratory depression, coma, and death. Reserve concomitant prescribing of DEMEROL Tablets and Oral Solution and benzodiazepines or other CNS depressants for use in patients for whom alternative treatment options are inadequate [see Warnings and Precautions (5.4), Drug Interactions (7)].

Neonatal Opioid Withdrawal Syndrome

If opioid use is required for an extended period of time in a pregnant woman, advise the patient of the risk of NOWS, which may be life-threatening if not recognized and treated. Ensure that management by neonatology experts will be available at delivery [see Warnings and Precautions (5.5)].

Opioid Analgesic Risk Evaluation and Mitigation Strategy (REMS)

Healthcare providers are strongly encouraged to complete a REMS-compliant education program and to counsel patients and caregivers on serious risks, safe use, and the importance of reading the Medication Guide with each prescription [see Warnings and Precautions (5.6)].

Cytochrome P450 3A4 (CYP3A4) Interaction

The concomitant use of DEMEROL Tablets or Oral Solution with all cytochrome P450 3A4 (CYP3A4) inhibitors may result in an increase in meperidine plasma concentrations, which could increase or prolong adverse reactions and may cause potentially fatal respiratory depression. In addition, discontinuation of a concomitantly used cytochrome P450 3A4 (CYP3A4) inducer may result in an increase in meperidine plasma concentration. Monitor patients receiving DEMEROL Tablets or Oral Solution, and any CYP3A4 inhibitor or inducer [see Warnings and Precautions (5.7), Drug Interactions (7)].

Concomitant use of DEMEROL Tablets and Oral Solution with Monoamine Oxidase Inhibitors (MAOIs)

Concomitant use of DEMEROL Tablets or Oral Solution with monoamine oxidase inhibitors (MAOIs) can result in coma, severe respiratory depression, cyanosis, and hypotension. Use of DEMEROL Tablets or Oral Solution with MAOIs within last 14 days is contraindicated [see Contraindications (4), Warnings and Precautions (5.8), Drug Interactions (7)].

1 INDICATIONS AND USAGE

DEMEROL Tablets and Oral Solution are indicated for the management of acute pain severe enough to require an opioid analgesic and for which alternative treatments are inadequate.

Limitations of Use

Because of the risks of addiction, abuse, and misuse with opioids, which can occur at any dosage or duration [see Warnings and Precautions (5.2)], reserve DEMEROL Tablets or Oral Solution for use in patients for whom alternative treatment options (e.g., non-opioid analgesics or opioid combination products):

- Have not been tolerated, or are not expected to be tolerated,
- Have not provided adequate analgesia, or are not expected to provide adequate analgesia.

DEMEROL Tablets and Oral Solution should not be used for an extended period of time unless the pain remains severe enough to require an opioid analgesic and for which alternative treatment options continue to be inadequate.

DEMEROL Tablets or Oral Solution should not be used for the treatment of chronic pain. Use of DEMEROL Tablet or Oral Solution for an extended period of time may increase the risk of toxicity (e.g., seizures) from the accumulation of the meperidine metabolite, normeperidine.

2 DOSAGE AND ADMINISTRATION

2.1 Important Dosage and Administration Instructions

DEMEROL Oral Solution

Ensure accuracy when prescribing, dispensing, and administering DEMEROL Oral Solution to avoid dosing errors due to confusion between mg and mL, and with other meperidine solutions of different concentrations, which could result in accidental overdose and death. Ensure the proper dose is communicated and dispensed. When writing prescriptions, include both the total dose in mg and the total dose in volume.

Instruct patients and caregivers on how to accurately measure and take or administer the correct dose of DEMEROL Oral Solution.

Strongly advise patients and caregivers to always use a graduated oral syringe or measuring cup, with metric units of measurements (i.e., mL), to correctly measure the prescribed amount of medication.

Inform patients and caregivers that oral dosing devices may be obtained from their pharmacy and to never use household teaspoons or tablespoons to measure DEMEROL Oral Solution.

DEMEROL Tablets and Oral Solution

DEMEROL Tablets and Oral Solution should be prescribed only by healthcare professionals who are knowledgeable about the use of opioids and how to mitigate the associated risks.

Use the lowest effective dosage for the shortest duration of time consistent with individual patient treatment goals [see Warnings and Precautions (5)]. Because the risk of overdose increases as opioid doses increase, reserve titration to higher doses of DEMEROL Tablets and Oral Solution for patients in whom lower doses are insufficiently effective and in whom the expected benefits of using a higher dose opioid clearly outweigh the substantial risks.

Many acute pain conditions (e.g., the pain that occurs with a number of surgical procedures or acute musculoskeletal injuries) require no more than a few days of an opioid analgesic. Clinical guidelines on opioid prescribing for some acute pain conditions are available.

There is variability in the opioid analgesic dose and duration needed to adequately manage pain due to both to the cause of pain and to individual patient factors. Initiate the dosing regimen for each patient individually, taking into account that patient’s underlying cause and severity of pain, prior analgesic treatment and response, and risk factors for addiction, abuse, and misuse [see Warnings and Precautions (5.1)].

Respiratory depression can occur at any time during opioid therapy, especially when initiating and following dosage increases with DEMEROL Tablets and Oral Solution. Consider this risk when selecting an initial dose and when making dose adjustments [see Warnings and Precautions (5)].

2.2 Patient Access to Naloxone for the Emergency Treatment of Opioid Overdose

Discuss the availability of naloxone for the emergency treatment of opioid overdose with the patient and caregiver and assess the potential need for access to naloxone, both when initiating and renewing treatment with DEMEROL Tablets or Oral Solution [see Warnings and Precautions (5.4)].

Inform patients and caregivers about the various ways to obtain naloxone as permitted by individual state naloxone dispensing and prescribing requirements or guidelines (e.g., by prescription, directly from a pharmacist, or as part of a community-based program).

Consider prescribing naloxone, based on the patient’s risk factors for overdose, such as concomitant use of CNS depressants, a history of opioid use disorder, or prior opioid overdose. The presence of risk factors for overdose should not prevent the proper management of pain in any given patient [see Warnings and Precautions (5.2, 5.4, 5.7)].

Consider prescribing naloxone if the patient has household members (including children) or other close contacts at risk for accidental ingestion or overdose.

2.3 Initial Dosage

Adults

Initiate treatment with DEMEROL Tablets or Oral Solution in a dosing range of 50 mg to 150 mg orally, every 3 or 4 hours as needed for pain, and at the lowest dose necessary to achieve adequate analgesia. Titrate the dose based upon the individual patient’s response to their initial dose of DEMEROL Tablets and Oral Solution.

Pediatric Patients

Initiate treatment with DEMEROL in a dosing range of 1.1 mg/kg to 1.8 mg/kg orally, up to the adult dose, every 3 or 4 hours as needed, at the lowest dose necessary to achieve adequate analgesia. Titrate the dose based upon the individual patient’s response to their initial dose of DEMEROL Tablets and Oral Solution.

2.4 Dosage Modification with Concomitant Use with Phenothiazines

The dose of DEMEROL Tablets or Oral Solution should be reduced by 25 to 50% when administered concomitantly with phenothiazines and other tranquilizers.

2.5 Titration and Maintenance of Therapy

Individually titrate DEMEROL Tablets and Oral Solution to a dose that provides adequate analgesia and minimizes adverse reactions. If adequate pain management cannot be achieved with a total daily dosage of 600 mg or less, discontinue treatment with DEMEROL Tablets or Oral Solution by tapering the dose and select an alternate analgesic.

Continually reevaluate patients receiving DEMEROL Tablets or Oral Solution to assess the maintenance of pain control, signs and symptoms of opioid withdrawal, and other adverse reactions, as well as to reassess for the development of addiction, abuse, or misuse [see Warnings and Precautions (5.2)]. Frequent communication is important among the prescriber, other members of the healthcare team, the patient, and the caregiver/family during periods of changing analgesic requirements, including initial titration.

If the level of pain increases after dosage stabilization, attempt to identify the source of increased pain before increasing the DEMEROL Tablets or Oral Solution dosage. If after increasing the dosage, unacceptable opioid-related adverse reactions are observed (including an increase in pain after a dosage increase), consider reducing the dosage [see Warnings and Precautions (5)]. Adjust the dosage to obtain an appropriate balance between management of pain and opioid-related adverse reactions.

2.6 Safe Reduction or Discontinuation of DEMEROL Tablets and Oral Solution

Do not abruptly discontinue DEMEROL Tablets and Oral Solution in patients who may be physically dependent on opioids. Rapid discontinuation of opioid analgesics in patients who are physically dependent on opioids has resulted in serious withdrawal symptoms, uncontrolled pain, and suicide. Rapid discontinuation has also been associated with attempts to find other sources of opioid analgesics, which may be confused with drug-seeking for abuse. Patients may also attempt to treat their pain or withdrawal symptoms with illicit opioids, such as heroin, and other substances.

When a decision has been made to decrease the dose or discontinue therapy in an opioid-dependent patient taking DEMEROL Tablets and Oral Solution, there are a variety of factors that should be considered, including the total daily dose of opioid (including DEMEROL Tablets and Oral Solution) the patient has been taking, the duration of treatment, the type of pain being treated, and the physical and psychological attributes of the patient. It is important to ensure ongoing care of the patient and to agree on an appropriate tapering schedule and follow-up plan so that patient and provider goals and expectations are clear and realistic. When opioid analgesics are being discontinued due to a suspected substance use disorder, evaluate and treat the patient, or refer for evaluation and treatment of the substance use disorder.

Treatment should include evidence-based approaches, such as medication assisted treatment of opioid use disorder. Complex patients with co-morbid pain and substance use disorders may benefit from referral to a specialist.

There are no standard opioid tapering schedules that are suitable for all patients. Good clinical practice dictates a patient-specific plan to taper the dose of the opioid gradually. For patients on DEMEROL Tablets and Oral Solution who are physically opioid-dependent, initiate the taper by a small enough increment (e.g., no greater than 10% to 25% of the total daily dose) to avoid withdrawal symptoms, and proceed with dose-lowering at an interval of every 2 to 4 weeks. Patients who have been taking opioids for briefer periods of time may tolerate a more rapid taper.

It may be necessary to provide the patient with lower dosage strengths to accomplish a successful taper. Reassess the patient frequently to manage pain and withdrawal symptoms, should they emerge. Common withdrawal symptoms include restlessness, lacrimation, rhinorrhea, yawning, perspiration, chills, myalgia, and mydriasis. Other signs and symptoms also may develop, including irritability, anxiety, backache, joint pain, weakness, abdominal cramps, insomnia, nausea, anorexia, vomiting, diarrhea, or increased blood pressure, respiratory rate, or heart rate. If withdrawal symptoms arise, it may be necessary to pause the taper for a period of time or raise the dose of the opioid analgesic to the previous dose, and then proceed with a slower taper. In addition, evaluate patients for any changes in mood, emergence of suicidal thoughts, or use of other substances.

When managing patients taking opioid analgesics, particularly those who have been treated for an extended period of time and/or with high doses for chronic pain, ensure that a multimodal approach to pain management, including mental health support (if needed), is in place prior to initiating an opioid analgesic taper. A multimodal approach to pain management may optimize the treatment of chronic pain, as well as assist with the successful tapering of the opioid analgesic [see Warnings and Precautions (5.16), Drug Abuse and Dependence (9.3)].

3 DOSAGE FORMS AND STRENGTHS

Tablets

- 50 mg scored tablet (white, round and convex with a stylized “W” on one side and “D” over “35” on the other side)
- 100 mg scored tablet (white, round and convex with a stylized “W” on one side and “D” over “37” on the other side)

Oral Solution

- Nonalcoholic, banana-flavored 50mg per 5mL (10 mg/mL), bottles of 16 fl. oz.

4 CONTRAINDICATIONS

DEMEROL Tablets and Oral Solution are contraindicated in patients with:

- Significant respiratory depression [see Warnings and Precautions (5.4)]
- Acute or severe bronchial asthma in an unmonitored setting or in the absence of resuscitative equipment [see Warnings and Precautions (5.9)]
- Concomitant use of monoamine oxidase inhibitors (MAOIs) or within 14 days of having taken an MAOI [see Drug Interactions (7)]
- Known or suspected gastrointestinal obstruction, including paralytic ileus [see Warnings and Precautions (5.14)]
- Hypersensitivity to meperidine or to any of other ingredients of the product (e.g., anaphylaxis) [see Adverse Reactions (6)]

5 WARNINGS AND PRECAUTIONS

5.1 Risks of Accidental Overdose and Death Due to Medication Errors

Dosing errors can result in accidental overdose and death. Avoid dosing errors that may result from confusion between mg and mL and confusion with meperidine solutions of different concentrations, when prescribing, dispensing, and administering DEMEROL Oral Solution. Ensure that the dose is communicated clearly and dispensed accurately.

Instruct patients and caregivers on how to measure and take or administer the correct dose of DEMEROL Oral Solution and to use extreme caution when measuring the dose. Strongly advise patients to obtain and always use a graduated device that can measure and deliver the prescribed dose accurately, and to never use household teaspoons or tablespoons to measure a dose because these are not accurate measuring devices [see Dosage and Administration (2.1)].

5.2 Addiction, Abuse, and Misuse

DEMEROL Tablets and Oral Solution contain meperidine, a Schedule II controlled substance. As an opioid, DEMEROL Tablets and Oral Solution expose users to the risks of addiction, abuse and misuse [see Drug Abuse and Dependence (9)].

Although the risk of addiction in any individual is unknown, it can occur in patients appropriately prescribed DEMEROL Tablets or Oral Solution. Addiction can occur at recommended dosages and if the drug is misused or abused.

Assess each patient’s risk for opioid addiction, abuse, or misuse prior to prescribing DEMEROL Tablets and Oral Solution, and reassess all patients receiving DEMEROL Tablets or Oral Solution for the development of these behaviors and conditions. Risks are increased in patients with a personal or family history of substance abuse (including drug or alcohol abuse or addiction) or mental illness (e.g., major depression). The potential for these risks should not, however, prevent the proper management of pain in any given patient.

Patients at increased risk may be prescribed opioids such as DEMEROL Tablets and Oral Solution, but use in such patients necessitates intensive counseling about the risks and proper use of DEMEROL Tablets and Oral Solution along with frequent reevaluation for signs of addiction, abuse, and misuse. Consider prescribing naloxone for the emergency treatment of opioid overdose [see Dosage and Administration (2.2), Warnings and Precautions (5.4)].

Opioids are sought for non-medical use and are subject to diversion from legitimate prescribed use. Consider these risks when prescribing or dispensing DEMEROL Tablets or Oral Solution. Strategies to reduce these risks include prescribing the drug in the smallest appropriate quantity and advising the patient on careful storage of the drug during the course of treatment and proper disposal of unused drug. Contact local state professional licensing board or state-controlled substances authority for information on how to prevent and detect abuse or diversion of this product.

DEMEROL Tablets have been reported as being abused by crushing, chewing, snorting, or injecting the dissolved product. These practices will result in the uncontrolled delivery of the opioid and pose a significant risk to the abuser that could result in overdose or death.

5.3 Life-Threatening Respiratory Depression

Serious, life-threatening, or fatal respiratory depression has been reported with the use of opioids, even when used as recommended. Respiratory depression, if not immediately recognized and treated, may lead to respiratory arrest and death. Management of respiratory depression may include close observation, supportive measures, and use of opioid antagonists, depending on the patient’s clinical status [see Overdosage (10)]. Carbon dioxide (CO2) retention from opioid-induced respiratory depression can exacerbate the sedating effects of opioids.

While serious, life-threatening, or fatal respiratory depression can occur at any time during the use of DEMEROL Tablets or Oral Solution, the risk is greatest during the initiation of therapy or following a dosage increase of DEMEROL Tablets or Oral Solution.

To reduce the risk of respiratory depression, proper dosing and titration of DEMEROL Tablets and Oral Solution are essential [see Dosage and Administration (2)]. Overestimating the DEMEROL Tablets or Oral Solution dosage when converting patients from another opioid product can result in a fatal overdose with the first dose.

Accidental ingestion of DEMEROL Tablets or Oral Solution, especially by children, can result in respiratory depression and death due to an overdose of meperidine.

Educate patients and caregivers on how to recognize respiratory depression and emphasize the importance of calling 911 or getting emergency medical help right away in the event of a known or suspected overdose.

Opioids can cause sleep-related breathing disorders including central sleep apnea (CSA) and sleep-related hypoxemia. Opioid use increases the risk of CSA in a dose-dependent fashion. In patients who present with CSA, consider decreasing the opioid dosage using best practices for opioid taper [see Dosage and Administration (2.6)].

Patient Access to Naloxone for the Emergency Treatment of Opioid Overdose

Discuss the availability of naloxone for the emergency treatment of opioid overdose with the patient and caregiver and assess the potential need for access to naloxone, both when initiating and renewing treatment with DEMEROL Tablets or Oral Solution. Inform patients and caregivers about the various ways to obtain naloxone as permitted by individual state naloxone dispensing and prescribing requirements or guidelines (e.g., by prescription, directly from a pharmacist, or as part of a community-based program). Educate patients and caregivers on how to recognize respiratory depression and emphasize the importance of calling 911 or getting emergency medical help, even if naloxone is administered.

Consider prescribing naloxone, based on the patient’s risk factors for overdose, such as concomitant use of CNS depressants, a history of opioid use disorder, or prior opioid overdose. The presence of risk factors for overdose should not prevent the proper management of pain in any given patient. Also consider prescribing naloxone if the patient has household members (including children) or other close contacts at risk for accidental ingestion or overdose. If naloxone is prescribed, educate patients and caregivers on how to treat with naloxone. [see Dosage and Administration (2.2), Warnings and Precautions (5.2, 5.4), Overdosage (10)].

5.4 Risks from Concomitant Use with Benzodiazepines or Other CNS Depressants

Profound sedation, respiratory depression, coma, and death may result from the concomitant use of DEMEROL Tablets or Oral Solution with benzodiazepines and/or other CNS depressants, including alcohol (e.g., non-benzodiazepine sedatives/hypnotics, anxiolytics, tranquilizers, muscle relaxants, general anesthetics, antipsychotics, other opioids). Because of these risks, reserve concomitant prescribing of these drugs for use in patients for whom alternative treatment options are inadequate.

Observational studies have demonstrated that concomitant use of opioid analgesics and benzodiazepines increases the risk of drug-related mortality compared to use of opioid analgesics alone. Because of similar pharmacological properties, it is reasonable to expect similar risk with the concomitant use of other CNS depressant drugs with opioid analgesics [see Drug Interactions (7)].

If the decision is made to prescribe a benzodiazepine or other CNS depressant concomitantly with an opioid analgesic, prescribe the lowest effective dosages and minimum durations of concomitant use. In patients already receiving an opioid analgesic, prescribe a lower initial dose of the benzodiazepine or other CNS depressant than indicated in the absence of an opioid, and titrate based on clinical response. If an opioid analgesic is initiated in a patient already taking a benzodiazepine or other CNS depressant, prescribe a lower initial dose of the opioid analgesic, and titrate based on clinical response. Inform patients and caregivers of this potential interaction and educate them on the signs and symptoms of respiratory depression (including sedation).

If concomitant use is warranted, consider prescribing naloxone for the emergency treatment of opioid overdose [see Dosage and Administration (2.2), Warnings and Precautions (5.4)].

Advise both patients and caregivers about the risks of respiratory depression and sedation when DEMEROL Tablets or Oral Solution is used with benzodiazepines or other CNS depressants (including alcohol and illicit drugs). Advise patients not to drive or operate heavy machinery until the effects of concomitant use of the benzodiazepine or other CNS depressant have been determined. Screen patients for risk of substance use disorders, including opioid abuse and misuse, and warn them of the risk for overdose and death associated with the use of additional CNS depressants including alcohol and illicit drugs [see Drug Interactions (7)].

5.5 Neonatal Opioid Withdrawal Syndrome

Use of DEMEROL Tablets and Oral Solution for an extended period of time during pregnancy can result in withdrawal in the neonate. Neonatal opioid withdrawal syndrome, unlike opioid withdrawal syndrome in adults, may be life-threatening if not recognized and treated, and requires management according to protocols developed by neonatology experts. Observe newborns for signs of neonatal opioid withdrawal syndrome and manage accordingly. Advise pregnant women using opioids for an extended period of time of the risk of neonatal opioid withdrawal syndrome and ensure that appropriate treatment will be available [see Use in Specific Populations (8.1)].

5.6 Opioid Analgesic Risk Evaluation and Mitigation Strategy (REMS)

To ensure that the benefits of opioid analgesics outweigh the risks of addiction, abuse, and misuse, the Food and Drug Administration (FDA) has required a Risk Evaluation and Mitigation Strategy (REMS) for these products. Under the requirements of the REMS, drug companies with approved opioid analgesic products must make REMS-compliant education programs available to healthcare providers. Healthcare providers are strongly encouraged to do all of the following:

- Complete a REMS-compliant education program offered by an accredited provider of continuing education (CE) or another education program that includes all the elements of the FDA Education Blueprint for Health Care Providers Involved in the Management or Support of Patients with Pain.
- Discuss the safe use, serious risks, and proper storage and disposal of opioid analgesics with patients and/or their caregivers every time these medications are prescribed. The Patient Counseling Guide (PCG) can be obtained at this link: www.fda.gov/OpioidAnalgesicREMSPCG.
- Emphasize to patients and their caregivers the importance of reading the Medication Guide that they will receive from their pharmacist every time an opioid analgesic is dispensed to them.
- Consider using other tools to improve patient, household, and community safety, such as patient-prescriber agreements that reinforce patient-prescriber responsibilities.

To obtain further information on the opioid analgesic REMS and for a list of accredited REMS CME/CE, call 1-800-503-0784, or log on to www.opioidanalgesicrems.com. The FDA Blueprint can be found at www.fda.gov/OpioidAnalgesicREMSBlueprint.

5.7 Risks of Concomitant Use or Discontinuation of Cytochrome P450 3A4 (CYP3A4) Inhibitors and Inducers

Concomitant use of DEMEROL Tablets or Oral Solution with a CYP3A4 inhibitor, such as macrolide antibiotics (e.g., erythromycin), azole-antifungal agents (e.g., ketoconazole), and protease inhibitors (e.g., ritonavir), may increase plasma concentrations of meperidine and prolong opioid adverse reactions, which may cause potentially fatal respiratory depression, particularly when an inhibitor is added after a stable dose of DEMEROL Tablets or Oral Solution is achieved. Similarly, discontinuation of a CYP3A4 inducer, such as rifampin, carbamazepine, and phenytoin, in DEMEROL Tablets or Oral Solution-treated patients may increase meperidine plasma concentrations and prolong opioid adverse reactions. When using DEMEROL and Oral Solution with CYP3A4 inhibitors or discontinuing CYP3A4 inducers in DEMEROL Tablets and Oral Solution-treated patients, evaluate patients at frequent intervals and consider dosage reduction of DEMEROL Tablets and Oral Solution until stable drug effects are achieved.

Concomitant use of DEMEROL Tablets or Oral Solution with CYP3A4 inducers or discontinuation of a CYP3A4 inhibitor could decrease meperidine plasma concentrations, decrease opioid efficacy or, possibly, lead to a withdrawal syndrome in a patient who had developed physical dependence to meperidine. When using DEMEROL Tablets and Oral Solution with CYP3A4 inducers or discontinuing CYP3A4 inhibitors, evaluate patients closely at frequent intervals and consider increasing the opioid dosage if needed to maintain adequate analgesia or if symptoms of opioid withdrawal occur [see Drug Interactions (7)].

5.8 Fatal Interaction with Monoamine Oxidase Inhibitors (MAOIs)

Meperidine is contraindicated in patients who are receiving monoamine oxidase inhibitors (MAOIs) or those who have recently received such agents. Therapeutic doses of meperidine have occasionally precipitated unpredictable, severe, and occasionally fatal reactions in patients who have received such agents within 14 days. The mechanism of these reactions is unclear, but may be related to a pre-existing hyperphenylalaninemia. Some have been characterized by coma, severe respiratory depression, cyanosis, and hypotension, and have resembled the syndrome of acute narcotic overdose. Serotonin syndrome with agitation, hyperthermia, diarrhea, tachycardia, sweating, tremors and impaired consciousness may also occur. In other reactions the predominant manifestations have been hyperexcitability, convulsions, tachycardia, hyperpyrexia, and hypertension.

Do not use DEMEROL Tablets and Oral Solution in patients taking MAOIs or within 14 days of stopping such treatment.

Intravenous hydrocortisone or prednisolone has been used to treat severe reactions, with the addition of intravenous chlorpromazine in those cases exhibiting hypertension and hyperpyrexia. The usefulness and safety of narcotic antagonists in the treatment of these reactions is unknown.

5.9 Opioid-Induced Hyperalgesia and Allodynia

Opioid-Induced Hyperalgesia (OIH) occurs when an opioid analgesic paradoxically causes an increase in pain, or an increase in sensitivity to pain. This condition differs from tolerance, which is the need for increasing doses of opioids to maintain a defined effect [see Dependence (9.3)]. Symptoms of OIH include (but may not be limited to) increased levels of pain upon opioid dosage increase, decreased levels of pain upon opioid dosage decrease, or pain from ordinarily non-painful stimuli (allodynia). These symptoms may suggest OIH only if there is no evidence of underlying disease progression, opioid tolerance, opioid withdrawal, or addictive behavior.

Cases of OIH have been reported, both with short-term and longer-term use of opioid analgesics. Though the mechanism of OIH is not fully understood, multiple biochemical pathways have been implicated. Medical literature suggests a strong biologic plausibility between opioid analgesics and OIH and allodynia. If a patient is suspected to be experiencing OIH, carefully consider appropriately decreasing the dose of the current opioid analgesic, or opioid rotation (safety switching the patient to a different opioid moiety) [see Dosage and Administration (2.6); Warnings and Precautions (5.17)].

5.10 Serotonin Syndrome with Concomitant Use of Serotonergic Drugs

Cases of serotonin syndrome, a potentially life-threatening condition, have been reported during concomitant use of DEMEROL Tablets or Oral Solution with serotonergic drugs. Serotonergic drugs include selective serotonin reuptake inhibitors (SSRIs), serotonin and norepinephrine reuptake inhibitors (SNRIs), St John’s wort, tricyclic antidepressants (TCAs), triptans, 5-HT3 receptor antagonists, drugs that affect the serotonergic neurotransmitter system (e.g., mirtazapine, trazodone, tramadol), certain muscle relaxants (i.e., cyclobenzaprine, metaxalone), and drugs that impair metabolism of serotonin (including MAOIs, both those intended to treat psychiatric disorders and also others, such as linezolid and intravenous methylene blue) [see Drug Interactions (7)]. This may occur within the recommended dosage range.

Serotonin syndrome symptoms may include mental status changes (e.g., agitation, hallucinations, coma), autonomic instability (e.g., tachycardia, labile blood pressure, hyperthermia), neuromuscular aberrations (e.g., hyperreflexia, incoordination, rigidity), and/or gastrointestinal symptoms (e.g., nausea, vomiting, diarrhea). The onset of symptoms generally occurs within several hours to a few days of concomitant use, but may occur later than that. Discontinue DEMEROL Tablets or Oral Solution if serotonin syndrome is suspected.

5.11 Life-Threatening Respiratory Depression in Patients with Chronic Pulmonary Disease or in Elderly, Cachectic, or Debilitated Patients

The use of DEMEROL Tablets or Oral Solution in patients with acute or severe bronchial asthma in an unmonitored setting or in the absence of resuscitative equipment is contraindicated.

Patients with Chronic Pulmonary Disease: DEMEROL Tablets or Oral Solution-treated patients with significant chronic obstructive pulmonary disease or cor pulmonale, and those with a substantially decreased respiratory reserve, hypoxia, hypercapnia, or pre-existing respiratory depression are at increased risk of decreased respiratory drive including apnea, even at recommended dosages of DEMEROL Tablets or Oral Solution [see Warnings and Precautions (5.2)].

Elderly, Cachectic, or Debilitated Patients: Life-threatening respiratory depression is more likely to occur in elderly, cachectic, or debilitated patients because they may have altered pharmacokinetics or altered clearance compared to younger, healthier patients [see Warnings and Precautions (5.2)].

Regularly evaluate patients, particularly when initiating and titrating DEMEROL Tablets and Oral Solution and when DEMEROL Tablets and Oral Solution are given concomitantly with other drugs that depress respiration [see Warnings and Precautions (5.3)], Drug Interactions (7)]. Alternatively, consider the use of non-opioid analgesics in these patients.

5.12 Adrenal Insufficiency

Cases of adrenal insufficiency have been reported with opioid use, more often following greater than one month of use. Presentation of adrenal insufficiency may include non-specific symptoms and signs including nausea, vomiting, anorexia, fatigue, weakness, dizziness, and low blood pressure. If adrenal insufficiency is suspected, confirm the diagnosis with diagnostic testing as soon as possible. If adrenal insufficiency is diagnosed, treat with physiologic replacement doses of corticosteroids. Wean the patient off of the opioid to allow adrenal function to recover and continue corticosteroid treatment until adrenal function recovers. Other opioids may be tried as some cases reported use of a different opioid without recurrence of adrenal insufficiency. The information available does not identify any particular opioids as being more likely to be associated with adrenal insufficiency.

5.13 Severe Hypotension

DEMEROL Tablets and Oral Solution may cause severe hypotension including orthostatic hypotension and syncope in ambulatory patients. There is increased risk in patients whose ability to maintain blood pressure has already been compromised by a reduced blood volume or concurrent administration of certain CNS depressant drugs (e.g., phenothiazines or general anesthetics) [see Drug Interactions (7)]. Regularly evaluate these patients for signs of hypotension after initiating or titrating the dosage of DEMEROL Tablets or Oral Solution. In patients with circulatory shock, DEMEROL Tablets and Oral Solution may cause vasodilation that can further reduce cardiac output and blood pressure. Avoid the use of DEMEROL Tablets or Oral Solution in patients with circulatory shock.

5.14 Risks of Use in Patients with Increased Intracranial Pressure, Brain Tumors, Head Injury, or Impaired Consciousness

In patients who may be susceptible to the intracranial effects of CO2 retention (e.g., those with evidence of increased intracranial pressure or brain tumors), DEMEROL Tablets and Oral Solution may reduce respiratory drive, and the resultant CO2 retention can further increase intracranial pressure. Monitor such patients for signs of sedation and respiratory depression, particularly when initiating therapy with DEMEROL Tablets or Oral Solution.

Opioids may also obscure the clinical course in a patient with a head injury. Avoid the use of DEMEROL Tablets or Oral Solution in patients with impaired consciousness or coma.

5.15 Risks of Use in Patients with Gastrointestinal Conditions

DEMEROL Tablets and Oral Solution are contraindicated in patients with known or suspected gastrointestinal obstruction, including paralytic ileus.

The meperidine in DEMEROL Tablets and Oral Solution may cause spasm of the sphincter of Oddi. Opioids may cause increases in serum amylase. Regularly evaluate patients with biliary tract disease, including acute pancreatitis, for worsening symptoms.

5.16 Increased Risk of Seizures in Patients with Seizure Disorders

The meperidine in DEMEROL Tablets and Oral Solution may increase the frequency of seizures in patients with seizure disorders, and may increase the risk of seizures occurring in other clinical settings associated with seizures. If dosage is escalated substantially above recommended levels because of tolerance development, seizures may occur in individuals without a history of seizures disorders. Regularly evaluate patients with a history of seizure disorders for worsened seizure control during DEMEROL Tablets and Oral Solution therapy. Use of DEMEROL Tablets and Oral Solution for an extended period of time may increase the risk of toxicity (e.g., seizures) from the accumulation of the meperidine metabolite, normeperidine.

5.17 Withdrawal

Do not abruptly discontinue DEMEROL Tablets or Oral Solution in a patient physically dependent on opioids. When discontinuing DEMEROL Tablets or Oral Solution in a physically dependent patient, gradually taper the dosage. Rapid tapering of meperidine in a patient physically dependent on opioids may lead to a withdrawal syndrome and return of pain [see Dosage and Administration (2.6), Drug Abuse and Dependence (9)].

Additionally, avoid the use of mixed agonist/antagonist (e.g., pentazocine, nalbuphine, and butorphanol) or partial agonist (e.g., buprenorphine) analgesics in patients who are receiving a full opioid agonist analgesic, including DEMEROL Tablets and Oral Solution. In these patients, mixed agonist/antagonist and partial agonist analgesics may reduce the analgesic effect and/or precipitate withdrawal symptoms [see Drug Interactions (7)].

5.18 Risks of Driving and Operating Machinery

DEMEROL Tablets and Oral Solution may impair the mental or physical abilities needed to perform potentially hazardous activities such as driving a car or operating machinery. Warn patients not to drive or operate dangerous machinery unless they are tolerant to the effects of DEMEROL Tablets or Oral Solution and know how they will react to the medication.

5.19 Risks in Patients with Pheochromocytoma

In patients with pheochromocytoma, DEMEROL Tablets and Oral Solution has been reported to provoke hypertension.

5.20 Risk of Use in Patients with Atrial Flutter and Other Supraventricular Tachycardias

Meperidine should be used with caution in patients with atrial flutter and other supraventricular tachycardias because of a possible vagolytic action which may produce a significant increase in the ventricular response rate.

6 ADVERSE REACTIONS

The following serious adverse reactions are described, or described in greater detail, in other sections:

- Addiction, Abuse, and Misuse [see Warnings and Precautions (5.2)]
- Life-Threatening Respiratory Depression [see Warnings and Precautions (5.3)]
- Interactions with Benzodiazepines or Other CNS Depressants [see Warnings and Precautions (5.4)]
- Neonatal Opioid Withdrawal Syndrome [see Warnings and Precautions (5.5)]
- Opioid-Induced Hyperalgesia and Allodynia [see Warnings and Precautions (5.9)]
- Serotonin Syndrome [see Warnings and Precautions (5.10)]
- Adrenal Insufficiency [see Warnings and Precautions (5.12)]
- Severe Hypotension [see Warnings and Precautions (5.13)]
- Gastrointestinal Adverse Reactions [see Warnings and Precautions (5.15)]
- Seizures [see Warnings and Precautions (5.16)]
- Withdrawal [see Warnings and Precautions (5.17)]

The following adverse reactions associated with the use of meperidine were identified in clinical studies or postmarketing reports. Because some of these reactions were reported voluntarily from a population of uncertain size, it is not always possible to reliably estimate their frequency or establish a causal relationship to drug exposure.

The major hazards of meperidine, as with other opioid analgesics, are respiratory depression and, to a lesser degree, circulatory depression, respiratory arrest, shock, and cardiac arrest.

The most frequently observed adverse reactions included lightheadedness, dizziness, sedation, nausea, vomiting, and sweating. These effects seem to be more prominent in ambulatory patients and in those who are not experiencing severe pain. In such individuals, lower doses are advisable. Some adverse reactions in ambulatory patients may be alleviated if the patient lies down.

Other adverse reactions include:

Nervous System: Mood changes (e.g., euphoria, dysphoria), weakness, headache, agitation, tremor, involuntary muscle movements (e.g., muscle twitches, myoclonus), severe convulsions, transient hallucinations and disorientation, confusion, delirium, visual disturbances.

Gastrointestinal: Dry mouth, constipation, biliary tract spasm.

Cardiovascular: Flushing of the face, tachycardia, bradycardia, palpitation, hypotension [see Warnings and Precautions (5.7)], syncope.

Genitourinary: Urinary retention.

Allergic: Pruritus, urticaria, other skin rashes, wheal and flare over the vein with intravenous injection. Hypersensitivity reactions, anaphylaxis.

Histamine release leading to hypotension and/or tachycardia, flushing, sweating, and pruritus.

Serotonin syndrome: Cases of serotonin syndrome, a potentially life-threatening condition, have been reported during concomitant use of opioids with serotonergic drugs.

Adrenal insufficiency: Cases of adrenal insufficiency have been reported with opioid use, more often following greater than one month of use.

Androgen deficiency: Cases of androgen deficiency have occurred with use of opioids for an extended period of time [see Clinical Pharmacology (12.2)].

Hyperalgesia and Allodynia: Cases of hyperalgesia and allodynia have been reported with opioid therapy of any duration [see Warnings and Precautions (5.9)].

Hypoglycemia: Cases of hypoglycemia have been reported in patients taking opioids. Most reports were in patients with at least one predisposing risk factor (e.g., diabetes).

To report SUSPECTED ADVERSE REACTIONS, contact Validus Pharmaceuticals LLC at 1-866-982-5438 or FDA at 1-800-FDA-1088 or www.fda.gov/medwatch.

7 DRUG INTERACTIONS

Table 1 includes clinically significant drug interactions with DEMEROL Tablets and Oral Solution.

Table 1: Clinically Significant Drug Interactions with DEMEROL Tablets and Oral Solution
Monoamine Oxidase Inhibitors (MAOIs)
Clinical Impact: | Meperidine is contraindicated in patients who are receiving monoamine oxidase (MAOIs) or those who have recently received such agents. Therapeutic doses of meperidine have occasionally precipitated unpredictable, severe, and occasionally fatal reactions in patients who have received such agents within 14 days. The mechanism of these reactions is unclear, but may be related to a preexisting hyperphenylalaninemia. Some have been characterized by coma, severe respiratory depression, cyanosis, and hypotension, and have resembled the syndrome of acute narcotic overdose. Serotonin syndrome with agitation, hyperthermia, diarrhea, tachycardia, sweating, tremors and impaired consciousness may also occur. In other reactions the predominant manifestations have been hyperexcitability, convulsions, tachycardia, hyperpyrexia, and hypertension.
Intervention: | Do not use DEMEROL Tablets or Oral Solution in patients taking MAOIs or within 14 days of stopping such treatment. Intravenous hydrocortisone or prednisolone have been used to treat severe reactions, with the addition of intravenous chlorpromazine in those cases exhibiting hypertension and hyperpyrexia. The usefulness and safety of narcotic antagonists in the treatment of these reactions is unknown.)
Examples: | phenelzine, tranylcypromine, linezolid
Inhibitors of CYP3A4 and CYP2B6
Clinical Impact: | The concomitant use of DEMEROL Tablets or Oral Solution and CYP3A4 or CYP2B6 inhibitors can increase the plasma concentration of meperidine, resulting in increased or prolonged opioid effects. These effects could be more pronounced with concomitant use of DEMEROL Tablets or Oral Solution and CYP2B6 and CYP3A4 inhibitors, particularly when an inhibitor is added after a stable dose of DEMEROL Tablets or Oral Solution is achieved [see Warnings and Precautions (5.6)]. After stopping a CYP3A4 or CYP2B6 inhibitor, as the effects of the inhibitor decline, the meperidine plasma concentration will decrease [see Clinical Pharmacology (12.3)], resulting in decreased opioid efficacy or a withdrawal syndrome in patients who had developed physical dependence to meperidine.
Intervention: | If concomitant use is necessary, consider dosage reduction of DEMEROL Tablets and Oral Solution until stable drug effects are achieved. Evaluate patients at frequent intervals for respiratory depression and sedation. If a CYP3A4 or CYP2B6 inhibitor is discontinued, consider increasing the DEMEROL Tablets and Oral Solution dosage until stable drug effects are achieved. Assess for signs of opioid withdrawal.
Examples | Macrolide antibiotics (e.g., erythromycin), azole-antifungal agents (e.g., ketoconazole), protease inhibitors (e.g., ritonavir)
CYP3A4 and CYP2B6 Inducers
Clinical Impact: | The concomitant use of DEMEROL Tablets or Oral Solution and CYP3A4 or CYP2B6 inducers can decrease the plasma concentration of meperidine [see Clinical Pharmacology (12.3)], resulting in decreased efficacy or onset of a withdrawal syndrome in patients who have developed physical dependence to meperidine [see Warnings and Precautions (5.6)]. After stopping a CYP3A4 or CYP2B6 inducer, as the effects of the inducer decline, the meperidine plasma concentration will increase [see Clinical Pharmacology (12.3)], which could increase or prolong both the therapeutic effects and adverse reactions, and may cause serious respiratory depression.
Intervention: | If concomitant use is necessary, consider increasing the DEMEROL Tablets and Oral Solution dosage until stable drug effects are achieved. Assess for signs of opioid withdrawal. If a CYP3A4 or CYP2B6 inducer is discontinued, consider DEMEROL Tablets and Oral Solution dosage reduction and evaluate patients at frequent intervals for signs of respiratory depression and sedation.
Examples: | Rifampin, carbamazepine, phenytoin
Benzodiazepines and Other Central Nervous System (CNS) Depressants
Clinical Impact: | Due to additive pharmacologic effect, the concomitant use of benzodiazepines or other CNS depressants, including alcohol, can increase the risk of hypotension, respiratory depression, profound sedation, coma, and death.
Intervention: | Reserve concomitant prescribing of these drugs for use in patients for whom alternative treatment options are inadequate. Limit dosages and durations to the minimum required. Inform patients and caregivers of this potential interaction and educate them on the signs and symptoms of respiratory depression (including sedation). If concomitant use is warranted, consider prescribing naloxone for the emergency treatment of opioid overdose [see Dosage and Administration (2.2), Warnings and Precautions (5.2, 5.4, 5.7)].
Examples: | Benzodiazepines and other sedatives/hypnotics, anxiolytics, tranquilizers, muscle relaxants, general anesthetics, antipsychotics, other opioids, alcohol
Serotonergic Drugs
Clinical Impact: | The concomitant use of opioids with other drugs that affect the serotonergic neurotransmitter system has resulted in serotonin syndrome [see Warnings and Precautions 5.10].
Intervention: | If concomitant use is warranted, frequently evaluate the patient, particularly during treatment initiation and dose adjustment. Discontinue DEMEROL Tablets and Oral Solution if serotonin syndrome is suspected.
Examples: | Selective serotonin reuptake inhibitors (SSRIs), serotonin and norepinephrine reuptake inhibitors (SNRIs), tricyclic antidepressants (TCAs), triptans, 5-HT3 receptor antagonists, drugs that effect the serotonin neurotransmitter system (e.g., mirtazapine, trazodone, tramadol), certain muscle relaxants (i.e., cyclobenzaprine, metaxalone), monoamine oxidase inhibitors (MAOIs) (those intended to treat psychiatric disorders and also others, such as linezolid and intravenous methylene blue)
Mixed Agonist/Antagonist and Partial Agonist Opioid Analgesics
Clinical Impact: | May reduce the analgesic effect of DEMEROL Tablets or Oral Solution and/or precipitate withdrawal symptoms.
Intervention: | Avoid concomitant use.
Examples: | butorphanol, nalbuphine, pentazocine, buprenorphine
Muscle Relaxants
Clinical Impact: | Meperidine may enhance the neuromuscular blocking action of skeletal muscle relaxants and produce an increased degree of respiratory depression.
Intervention: | Because respiratory depression that may be greater than otherwise expected, decrease the dosage of DEMEROL Tablets and Oral Solution and/or the muscle relaxant as necessary. Due to the risk of respiratory depression with concomitant use of skeletal muscle relaxants and opioids, consider prescribing naloxone for the emergency treatment of opioid overdose [see Dosage and Administration (2.2), Warnings and Precautions (5.4, 5.7)].
Diuretics
Clinical Impact: | Opioids can reduce the efficacy of diuretics by inducing the release of antidiuretic hormone.
Intervention: | Evaluate patients for signs of diminished diuresis and/or effects on blood pressure and increase the dosage of the diuretic as needed.
Anticholinergic Drugs
Clinical Impact: | The concomitant use of anticholinergic drugs may increase risk of urinary retention and/or severe constipation, which may lead to paralytic ileus.
Intervention: | Evaluate patients for signs of urinary retention or reduced gastric motility when DEMEROL Tablets and Oral Solution is used concomitantly with anticholinergic drugs.
Acyclovir
Clinical Impact: | The concomitant use of acyclovir may increase the plasma concentrations of meperidine and its metabolite, normeperidine.
Intervention: | If concomitant use of acyclovir and DEMEROL Tablets and Oral Solution is necessary, evaluate patients for respiratory depression and sedation at frequent intervals.
Cimetidine
Clinical Impact: | The concomitant use of cimetidine may reduce the clearance and volume of distribution of meperidine also the formation of the metabolite, normeperidine, in healthy subjects.
Intervention: | If concomitant use of cimetidine and DEMEROL Tablets and Oral Solution is necessary, evaluate patients for respiratory depression and sedation at frequent intervals.

8 USE IN SPECIFIC POPULATIONS

8.1 Pregnancy

Risk Summary

Use of opioid analgesics for an extended period of time during pregnancy may cause neonatal opioid withdrawal syndrome [see Warnings and Precautions (5.5)]. Available data with DEMEROL Tablets or Oral Solution are insufficient to inform a drug-associated risk for major birth defects and miscarriage or adverse maternal outcomes. Formal animal reproduction studies have not been conducted with meperidine. Neural tube defects (exencephaly and cranioschisis) have been reported in hamsters administered a single bolus dose of meperidine during a critical period of organogenesis at 0.85 and 1.5 times the total human daily dose of 1200 mg [see Data].

The background risk of major birth defects and miscarriage for the indicated population is unknown. All pregnancies have a background risk of birth defects, loss or other adverse outcomes. In the U.S. general population, the estimated background risk of major birth defects and miscarriage in clinically recognized pregnancies is 2 to 4% and 15 to 20%, respectively.

Clinical Considerations

Fetal/Neonatal Adverse Reactions

Use of opioid analgesics for an extended period of time during pregnancy for medical or nonmedical purposes can result in physical dependence in the neonate and neonatal opioid withdrawal syndrome shortly after birth.

Neonatal opioid withdrawal syndrome presents as irritability, hyperactivity and abnormal sleep pattern, high pitched cry, tremor, vomiting, diarrhea, and failure to gain weight. The onset, duration, and severity of neonatal opioid withdrawal syndrome vary based on the specific opioid used, duration of use, timing and amount of last maternal use, and rate of elimination of the drug by the newborn. Observe newborns for symptoms of neonatal opioid withdrawal syndrome and manage accordingly [see Warnings and Precautions (5.5)].

Labor or Delivery

Opioids cross the placenta and may produce respiratory depression and psycho-physiologic effects in neonates. Resuscitation may be required [see Overdose (10)]. An opioid antagonist, such as naloxone, must be available for reversal of opioid-induced respiratory depression in the neonate. DEMEROL Tablets and Oral Solution are not recommended for use in pregnant women during or immediately prior to labor, when other analgesic techniques are more appropriate. Opioid analgesics, including DEMEROL Tablets or Oral Solution, can prolong labor through actions which temporarily reduce the strength, duration, and frequency of uterine contractions. However, this effect is not consistent and may be offset by an increased rate of cervical dilation, which tends to shorten labor. Monitor neonates exposed to opioid analgesics during labor for signs of excess sedation and respiratory depression.

Data

Animal Data

Formal reproductive and developmental toxicology studies for meperidine have not been completed.

In a published study, neural tube defects (exencephaly and cranioschisis) were noted following subcutaneous administration of meperidine hydrochloride (127 and 218 mg/kg, respectively) on Gestation Day 8 to pregnant hamsters (0.85 and 1.5 times the total daily dose of 1200 mg/day based on body surface area). The findings cannot be clearly attributed to maternal toxicity.

8.2 Lactation

Risk Summary

Meperidine appears in the milk of nursing mothers receiving the drug. The developmental and health benefits of breastfeeding should be considered along with the mother’s clinical need for DEMEROL Tablets or Oral Solution and any potential adverse effects on the breastfed infant from DEMEROL Tablets or Oral Solution or from the underlying maternal condition.

Clinical Considerations

Monitor infants exposed to DEMEROL Tablets or Oral Solution through breast milk for excess sedation and respiratory depression. Withdrawal symptoms can occur in breast-fed infants when maternal administration of an opioid analgesic is stopped, or when breast-feeding is stopped.

8.3 Females and Males of Reproductive Potential

Infertility

Use of opioids for an extended period of time may cause reduced fertility in females and males of reproductive potential. It is not known whether these effects on fertility are reversible [see Adverse Reactions (6), Clinical Pharmacology (12.2)], Nonclinical Toxicology (13.1)].

8.4 Pediatric Use

The safety and effectiveness of meperidine in pediatric patients has not been established. Literature reports indicate that meperidine has a slower elimination rate in neonates and young infants compared to older children and adults. Neonates and young infants may also be more susceptible to the effects, especially the respiratory depressant effects. If meperidine use is contemplated in neonates or young infants, any potential benefits of the drug need to be weighed against the relative risk of the patient.

8.5 Geriatric Use

Clinical studies of DEMEROL Tablets and Oral Solution during product development did not include sufficient numbers of subjects aged 65 and over to evaluate age-related differences in safety or efficacy. Literature reports indicate that geriatric patients have a slower elimination rate compared to young patients and they may be more susceptible to the effects of meperidine. Reducing the total daily dose of meperidine is recommended in elderly patients, and the potential benefits of the drug should be weighed against the relative risk to a geriatric patient.

Respiratory depression is the chief risk for elderly patients treated with opioids, and has occurred after large initial doses were administered to patients who were not opioid-tolerant or when opioids were co-administered with other agents that depress respiration. Titrate the dosage of DEMEROL slowly in geriatric patients and frequent reevaluate the patient for signs of central nervous system and respiratory depression [see Warnings and Precautions (5.11)].

Meperidine is known to be substantially excreted by the kidney, and the risk of adverse reactions to this drug may be greater in patients with impaired renal function. Because elderly patients are more likely to have decreased renal function, care should be taken in dose selection, and it may be useful to regularly evaluate renal function.

8.6 Hepatic Impairment

Accumulation of meperidine and/or its active metabolite, normeperidine, can occur in patients with hepatic impairment. Elevated serum levels have been reported to cause central nervous system excitatory effects. Meperidine should therefore be used with caution in patients with hepatic impairment. Titrate the dosage of DEMEROL Tablets or Oral Solution slowly in patients with hepatic impairment and regularly evaluate for signs of central nervous system and respiratory depression.

8.7 Renal Impairment

Accumulation of meperidine and/or its active metabolite, normeperidine, can also occur in patients with renal impairment. Meperidine should therefore be used with caution in patients with renal impairment. Titrate the dosage of DEMEROL Tablets or Oral Solution slowly in patients with renal impairment and regularly evaluate for signs of central nervous system and respiratory depression.

9 DRUG ABUSE AND DEPENDENCE

9.1 Controlled Substance

DEMEROL Tablets and Oral Solution contain meperidine, a Schedule II controlled substance.

9.2 Abuse

DEMEROL Tablets and Oral Solution contain meperidine, a substance with a high potential for misuse and abuse, which can lead to the development of substance use disorder, including addiction [see Warnings and Precautions (5.2)].

Misuse is the intentional use, for therapeutic purposes, of a drug by an individual in a way other than prescribed by a health care provider or for whom it was not prescribed.

Abuse is the intentional, non-therapeutic use of a drug, even once, for its desirable psychological or physiological effects.

Drug addiction is a cluster of behavioral, cognitive, and physiological phenomena that may lead to central nervous system and respiratory depression, hypotension, seizures, and death. The risk is increased with concurrent abuse of DEMEROL Tablets and Oral Solution with alcohol and/or other CNS depressants. Abuse of an addiction to opioids in some individuals may not be accompanied by concurrent tolerance and symptoms of physical dependence. In addition, abuse of opioids can occur in the absence of addiction.

All patients treated with opioids require careful and frequent re-evaluation for signs of misuse, abuse, and addiction, because use of opioid analgesic products carries the risk of addiction even under appropriate medical use. Patients at high risk of DEMEROL Tablets and Oral Solution abuse include those with a history of prolonged use of products containing meperidine, those with a history of drug or alcohol abuse, or those who use DEMEROL Tablets and Oral Solution in combination with other abused drugs.

“Drug-seeking” behavior is very common in persons with substance use disorders. Drug-seeking tactics include emergency calls or visits near the end of office hours, refusal to undergo appropriate examination, testing, or referral, repeated “loss” of prescriptions, tampering with prescriptions, and reluctance to provide prior medical records or contact information for other treating healthcare provider(s). “Doctor shopping” (visiting multiple prescribers to obtain additional prescriptions) is common among people who abuse drugs and people with substance use disorder. Preoccupation with achieving adequate pain relief can be appropriate behavior in a patient with inadequate pain control.

DEMEROL Tablets and Oral Solution, like other opioids, can be diverted for non-medical use into illicit channels of distribution. Careful record-keeping of prescribing information, including quantity, frequency, and renewal requests, as required by state and federal law, is strongly advised.

Proper assessment of the patient, proper prescribing practices, periodic re-evaluation of therapy, and proper dispensing and storage are appropriate measures that help to limit abuse of opioid drugs.

Risks Specific to Abuse of DEMEROL Tablets and Oral Solution

Abuse of DEMEROL Tablets and Oral Solution poses a risk of overdose and death. The risk in increased with concurrent use of DEMEROL Tablets and Oral Solution with alcohol and/or other CNS depressants.

DEMEROL Tablets and Oral Solution is approved for oral use only.

DEMEROL Tablets have been reported as being abused by crushing, chewing, snorting, or injecting the dissolved product. Inappropriate intravenous, intramuscular, or subcutaneous use of DEMEROL Tablets or Oral Solution can result in death, local tissue necrosis, infection, pulmonary granulomas, increased risk of endocarditis, and valvular heart injury, and embolism.

Parenteral drug abuse is commonly associated with transmission of infectious diseases such as hepatitis and HIV.

9.3 Dependence

Both tolerance and physical dependence can develop during use of opioid therapy.

Tolerance is a physiological state characterized by a reduced response to a drug after repeated administration (i.e., a higher dose of a drug is required to product the same effect that was once obtained at a lower dose).

Physical dependence is a state that develops as a result of a physiological adaption in response to repeated drug use, manifested by withdrawal signs and symptoms after abrupt discontinuation or a significant dose reduction of a drug.

Withdrawal may be precipitated through the administration of drugs with opioid antagonist activity (e.g., naloxone), mixed agonist/antagonist analgesics (e.g., pentazocine, butorphanol, nalbuphine), or partial agonists (e.g., buprenorphine). Physical dependence may not occur to a clinically significant degree until after several days to weeks of continued use.

Do not abruptly discontinue DEMEROL Tablets and Oral Solution in a patient physically dependent on opioids. Rapid tapering of DEMEROL Tablets and Oral Solution in a patient physically dependent on opioids may lead to serious withdrawal symptoms, uncontrolled pain, and suicide. Rapid discontinuation has also been associated with attempts to find other sources of opioid analgesics, which may be confused with drug-seeking for abuse.

When discontinuing DEMEROL Tablets and Oral Solution, gradually taper the dosage using a patient-specific plan that considers the following: the dose of DEMEROL Tablets and Oral Solution the patient has been taking, the duration of treatment, and the physical and psychological attributes of the patient. To improve the likelihood of a successful taper and minimize withdrawal symptoms, it is important that the opioid tapering schedule is agreed upon by the patient. In patients taking opioids for an extended period of time at high doses, ensure that a multimodal approach to pain management, including mental health support (if needed), is in place prior to initiating an opioid analgesic taper [see Dosage and Administration (2.6), Warnings and Precautions (5.17)].

Infants born to mothers physically dependent on opioids will also be physically dependent and may exhibit respiratory difficulties and withdrawal signs [see Use in Specific Populations (8.1)].

10 OVERDOSAGE

Clinical Presentation

Acute overdose with meperidine can be manifested by respiratory depression, somnolence progressing to stupor or coma, skeletal muscle flaccidity, cold and clammy skin, constricted pupils, and, in some cases, pulmonary edema, bradycardia, hypotension, hypoglycemia, partial or complete airway obstruction, atypical snoring, and death. Marked mydriasis rather than miosis may be seen with hypoxia in overdose situations [see Clinical Pharmacology (12.2)].

Accumulation of normeperidine as in chronic use or possibly following introduction of a concomitant CYP3A4 inducer presents as excitatory syndrome including hallucinations, tremors, muscle twitches, dilated pupils, hyperactive reflexes, and convulsions.

Treatment of Overdose

In case of overdose, priorities are the reestablishment of a patent and protected airway and institution of assisted or controlled ventilation, if needed. Employ other supportive measures (including oxygen and vasopressors) in the management of circulatory shock and pulmonary edema as indicated. Cardiac arrest or arrhythmias will require advanced life-support measures.

Opioid antagonists, such as naloxone, are specific antidotes to respiratory depression resulting from opioid overdose. For clinically significant respiratory or circulatory depression secondary to meperidine overdose, administer an opioid antagonist.

Because the duration of opioid reversal is expected to be less than the duration of action of meperidine in DEMEROL Tablets and Oral Solution, carefully monitor the patient until spontaneous respiration is reliably reestablished. If the response to an opioid antagonist is suboptimal or only brief in nature, administer additional antagonist as directed by the product’s prescribing information.

In an individual physically dependent on opioids, administration of the recommended usual dosage of the antagonist will precipitate an acute withdrawal syndrome. The severity the withdrawal symptoms experienced will depend on the degree of physical dependence and the dose of antagonist administered. If a decision is made to treat serious respiratory depression in the physically dependent patient, administration of the antagonist should be initiated with care and by titration with smaller than usual doses of the antagonist.

11 DESCRIPTION

DEMEROL (meperidine hydrochloride, USP) Tablet and Oral Solution are opioid agonists. DEMEROL Tablets are available as 50 mg and 100 mg Tablets for oral administration. The chemical name is 4-Piperidinecarboxylic acid, 1-methyl-4-phenyl-, ethyl ester, hydrochloride. The molecular weight is 283,80. Its molecular formula is C15H21NO2·HCl, and it has the following chemical structure.

Meperidine hydrochloride is a white crystalline substance with a melting point of 186°C to 189°C. It is readily soluble in water and has a neutral reaction and a slightly bitter taste. The solution is not decomposed by a short period of boiling.

The Tablets contain 50 mg or 100 mg of meperidine hydrochloride.

The DEMEROL Oral Solution is a pleasant-tasting, nonalcoholic, banana-flavored solution containing 50 mg of meperidine hydrochloride, per 5 mL (10 mg/mL).

The Inactive Ingredients in DEMEROL Tablets include: Calcium Sulfate, Dibasic Calcium Phosphate, Starch, Stearic Acid, and Talc. The Tablets are white, round and convex. The 50 mg is a scored tablet and has a stylized “W” on one side and “D” over “35” on the other side. The 100 mg is a scored tablet and has a stylized “W” on one side and “D” over “37” on the other side.

The Inactive Ingredients in DEMEROL Oral Solution include: Benzoic Acid, Flavor, Liquid Glucose, Purified Water, Saccharin Sodium.

12 CLINICAL PHARMACOLOGY

12.1 Mechanism of Action

Meperidine is an opioid agonist with multiple actions qualitatively similar to those of morphine; the most prominent of these involve the central nervous system and organs composed of smooth muscle. The principal actions of therapeutic value are analgesia and sedation.

12.2 Pharmacodynamics

Effects on the Central Nervous System

Meperidine produces respiratory depression by direct action on brain stem respiratory centers. The respiratory depression involves a reduction in the responsiveness of the brain stem respiratory centers to both increases in carbon dioxide tension and electrical stimulation.

Meperidine causes miosis, even in total darkness. Pinpoint pupils are a sign of opioid overdose but are not pathognomonic (e.g., pontine lesions of hemorrhagic or ischemic origins may produce similar findings). Marked mydriasis rather than miosis may be seen due to hypoxia in overdose situations.

Effects on the Gastrointestinal Tract and Other Smooth Muscle

Meperidine causes a reduction in motility associated with an increase in smooth muscle tone in the antrum of the stomach and duodenum. Digestion of food in the small intestine is delayed and propulsive contractions are decreased. Propulsive peristaltic waves in the colon are decreased, while tone may be increased to the point of spasm, resulting in constipation. Other opioid-induced effects may include a reduction in biliary and pancreatic secretions, spasm of sphincter of Oddi, and transient elevations in serum amylase.

Effects on the Cardiovascular System

Meperidine produces peripheral vasodilation, which may result in orthostatic hypotension or syncope. Manifestations of histamine release and/or peripheral vasodilation may include pruritus, flushing, red eyes, sweating, and/or orthostatic hypotension.

Effects on the Endocrine System

Opioids inhibit the secretion of adrenocorticotropic hormone (ACTH), cortisol, and luteinizing hormone (LH) in humans [see Adverse Reactions (6)]. They also stimulate prolactin, growth hormone (GH) secretion, and pancreatic secretion of insulin and glucagon.

Use of opioids for an extended period of time may influence the hypothalamic-pituitary-gonadal axis, leading to androgen deficiency that may manifest as low libido, impotence, erectile dysfunction, amenorrhea, or infertility. The causal role of opioids in the clinical syndrome of hypogonadism is unknown because the various medical, physical, lifestyle, and psychological stressors that may influence gonadal hormone levels have not been adequately controlled for in studies conducted to date [see Adverse Reactions (6)].

Effects on the Immune System

Opioids have been shown to have a variety of effects on components of the immune system in vitro and animal models. The clinical significance of these findings is unknown. Overall, the effects of opioids appear to be modestly immunosuppressive.

Concentration–Efficacy Relationships

The minimum effective analgesic concentration will vary widely among patients, especially among patients who have been previously treated with opioids agonist opioids. The minimum effective analgesic concentration of meperidine for any individual patient may increase over time due to an increase in pain, the development of a new pain syndrome, and/or the development of analgesic tolerance [see Dosage and Administration (2.1)].

Concentration–Adverse Reaction Relationships

There is a relationship between increasing meperidine plasma concentration and increasing frequency of dose-related opioid adverse reactions such as nausea, vomiting, CNS effects, and respiratory depression. In opioid-tolerant patients, the situation may be altered by the development of tolerance to opioid-related adverse reactions [see Dosage and Administration (2.1)].

12.3 Pharmacokinetics

Absorption

Oral bioavailability of meperidine is approximately 50%.

Elimination

The elimination half-life is 3 to 8 hours in healthy volunteers. The only bioactive metabolite is normeperidine which has an average elimination half-life of 20.6 hours.

Metabolism

Meperidine is metabolized through biotransformation. In vitro data show meperidine is metabolized to normeperidine in liver mainly by CYP3A4 and CYP2B6.

Excretion

Meperidine and normeperidine are excreted by kidneys.

Age

In clinical studies reported in the literature, changes in several pharmacokinetic parameters with increasing age have been observed. The initial volume of distribution and steady-state volume of distribution may be higher in elderly patients than in younger patients. The free fraction of meperidine in plasma may be higher in patients over 45 years of age than in younger patients.

Hepatic impairment

The elimination half-life is 3 to 8 hours in healthy volunteers and is 1.3 to 2 times greater in post-operative or cirrhotic patients.

Drug Interactions Studies

Phenytoin

The hepatic metabolism of meperidine may be enhanced by phenytoin. Concomitant administration resulted in reduced half-life and bioavailability with increased clearance of meperidine in healthy subjects; however, blood concentrations of normeperidine were increased [see Drug Interactions (7)].

Ritonavir

Plasma concentrations of the active metabolite normeperidine may be increased by ritonavir [see Drug Interactions (7)].

Acyclovir

Plasma concentrations of meperidine and its metabolite, normeperidine, may be increased by acyclovir [see Drug Interactions (7)].

Cimetidine

Cimetidine reduced the clearance and volume of distribution of meperidine and also the formation of the metabolite, normeperidine, in healthy subjects [see Drug Interactions (7)].

13 NONCLINICAL TOXICOLOGY

13.1 Carcinogenesis, Mutagenesis, Impairment of Fertility

Carcinogenesis

Long-term studies in animals to evaluate the carcinogenic potential of meperidine have not been conducted.

Mutagenesis

Studies to in animals to evaluate the mutagenic potential of meperidine have not been conducted.

Impairment of Fertility

Studies to determine the effect of meperidine on fertility have not been conducted.

16 HOW SUPPLIED/STORAGE AND HANDLING

DEMEROL (meperidine hydrochloride) Tablets 50 mg, are white, round, convex scored tablets debossed with “W” on one side and “D” over “35” on the other, and are supplied as: HDPE plastic bottles of 100 (NDC Number 30698-335-01)

DEMEROL (meperidine hydrochloride) Tablets 100 mg, are white, round, convex scored Tablets debossed with “W” on one side and “D” over “37” on the other, and are supplied as: HDPE plastic bottles of 100 (NDC Number 30698-337-01)

DEMEROL (meperidine hydrochloride) Oral Solution, 50mg per 5mL (10 mg/mL) is non-alcoholic, banana-flavored syrup, and is supplied in 16 fl. oz. bottles (NDC Number 30698-332-16).

Store at 77°F (25°C); excursions permitted to 59° to 86°F (15° to 30°C) [See USP Controlled Room Temperature].

Store DEMEROL Tablets and Oral Solution securely and dispose of properly.

17 PATIENT COUNSELING INFORMATION

Advise the patient to read the FDA-approved patient labeling (Medication Guide).

Storage and Disposal

Because of the risks associated with accidental ingestion, misuse, and abuse, advise patients to store DEMEROL Tablets and Oral Solution securely, out of sight and reach of children, and in a location not accessible by others, including visitors to the home. Inform patients that leaving DEMEROL Tablets and Oral Solution unsecured can pose a deadly risk to others in the home [see Warnings and Precautions (5.1, 5.2), Drug Abuse and Dependence (9)].

Advise patients and caregivers that when medicines are no longer needed, they should be disposed of promptly. Expired, unwanted, or unused DEMEROL Tablets and Oral Solution should be disposed of by flushing the unused medication down the toilet if a drug take-back option is not readily available. Inform patients that they can visit www.fda.gov/drugdisposal for a complete list of medicines recommended for disposal by flushing, as well as additional information on disposal of unused medicines

Medication Errors

Strongly advise patients and caregivers to always use a graduated oral syringe or measuring cup, with metric units of measurements (i.e., mL), to correctly measure the prescribed amount of medication.

Inform patients and caregivers that oral dosing devices may be obtained from their pharmacy and to never use household teaspoons or tablespoons to measure DEMEROL Oral Solution [see Warnings and Precautions (5.1)].

If the prescribed dosage is changed, instruct patients and caregivers on how to correctly measure the new dose to avoid errors which could result in accidental overdose and death.

Addiction, Abuse, and Misuse

Inform patients that the use of DEMEROL Tablets or Oral Solution, even when taken as recommended, can result in addiction, abuse, and misuse, which can lead to overdose and death [see Warnings and Precautions (5.2)]. Instruct patients not to share DEMEROL Tablets or Oral Solution with others and to take steps to protect DEMEROL Tablets or Oral Solution from theft or misuse.

Life-Threatening Respiratory Depression

Inform patients of the risk of life-threatening respiratory depression, including information that the risk is greatest when starting DEMEROL Tablets or Oral Solution or when the dosage is increased, and that it can occur even at recommended dosages.

Educate patients and caregivers on how to recognize respiratory depression and emphasize the importance of calling 911 or getting emergency medical help right away in the event of a known or suspected overdose [see Warnings and Precautions (5.4)].

Accidental Ingestion

Inform patients that accidental ingestion, especially by children, may result in respiratory depression or death [see Warnings and Precautions (5.4)].

Interactions with Benzodiazepines and Other CNS Depressants

Inform patients and caregivers that potentially fatal additive effects may occur if DEMEROL Tablets or Oral Solution are used with benzodiazepines or other CNS depressants, including alcohol, and not to use these concomitantly unless supervised by a healthcare provider [see Warnings and Precautions (5.7), Drug Interactions (7)].

Patient Access to Naloxone for the Emergency Treatment of Opioid Overdose

Discuss with the patient and caregiver the availability of naloxone for the emergency treatment of opioid overdose, both when initiating and renewing treatment with DEMEROL Tablets or Oral Solution. Inform patients and caregivers about the various ways to obtain naloxone as permitted by individual state naloxone dispensing and prescribing requirements or guidelines (e.g., by prescription, directly from a pharmacist, or as part of a community-based program) [see Dosage and Administration (2.2), Warnings and Precautions (5.4)].

Educate patients and caregivers on how to recognize the signs and symptoms of an overdose.

Explain to patients and caregivers that naloxone’s effects are temporary, and that they must call 911 or get emergency medical help right away in all cases of known or suspected opioid overdose, even if naloxone is administered [see Overdosage (10)].

If naloxone is prescribed, also advise patients and caregivers:

• How to treat with naloxone in the event of an opioid overdose

• To tell family and friends about their naloxone and to keep it in a place where family and friends can access it in an emergency

• To read the Patient Information (or other educational material) that will come with their naloxone. Emphasize the importance of doing this before an opioid emergency happens, so the patient and caregiver will know what to do.

MAOI Interaction

Inform patients not to take DEMEROL Tablets or Oral Solution while using any drugs that inhibit monoamine oxidase. Patients should not start MAOIs while taking DEMEROL Tablets or Oral Solution [see Warnings and Precautions (5.8), Drug Interactions (7)].

Hyperalgesia and Allodynia

Inform patients and caregivers not to increase opioid dosage without first consulting a clinician. Advise patients to seek medical attention if they experience symptoms of hyperalgesia, including worsening pain, increased sensitivity to pain, or new pain [see Warnings and Precautions (5.9); Postmarketing Experience (6.2)].

Serotonin Syndrome

Inform patients that opioids could cause a rare but potentially life-threatening condition resulting from concomitant administration of serotonergic drugs. Warn patients of the symptoms of serotonin syndrome and to seek medical attention right away if symptoms develop. Instruct patients to inform their healthcare providers if they are taking, or plan to take serotonergic medications. [see Warnings and Precautions (5.10), Drug Interactions (7)].

Important Administration Instructions

Instruct patients how to properly take DEMEROL Tablets or Oral Solution [see Dosage and Administration (2.1), Warnings and Precautions (5.1)].

- Strongly advise patients and caregivers to always use a graduated oral syringe/dosing cup when administering DEMEROL Oral Solution to correctly measure the prescribed amount of medication [see Warnings and Precautions (5.1)].
- Instruct patients and caregivers to never use household teaspoon or tablespoon to measure DEMEROL Oral Solution.
- Instruct patients and caregivers not to adjust the dose of DEMEROL Tablets or Oral Solution without consulting with a physician or other healthcare professional.
- Instruct patients and caregivers to dilute each dose of DEMEROL oral solution in one-half glass of water because the undiluted solution may exert a slight topical anesthetic effect on mucous membranes.

Important Discontinuation Instructions

In order to avoid developing withdrawal symptoms, instruct patients not to discontinue DEMEROL Tablets and Oral Solution without first discussing a tapering plan with the prescriber [see Dosage and Administration (2.6)].

Driving or Operating Heavy Machinery

Inform patients that DEMEROL Tablets and Oral Solution may impair the ability to perform potentially hazardous activities such as driving a car or operating heavy machinery. Advise patients not to perform such tasks until they know how they will react to the medication [see Warnings and Precautions (5.17)].

Constipation

Advise patients of the potential for severe constipation, including management instructions and when to seek medical attention [see Adverse Reactions (6)].

Adrenal Insufficiency

Inform patients that opioids could cause adrenal insufficiency, a potentially life-threatening condition. Adrenal insufficiency may present with non-specific symptoms and signs such as nausea, vomiting, anorexia, fatigue, weakness, dizziness, and low blood pressure. Advise patients to seek medical attention if they experience a constellation of these symptoms [see Warnings and Precautions (5.11)].

Hypotension

Inform patients that DEMEROL Tablets or Oral Solution may cause orthostatic hypotension and syncope. Instruct patients how to recognize symptoms of low blood pressure and how to reduce the risk of serious consequences should hypotension occur (e.g., sit or lie down, carefully rise from a sitting or lying position) [see Warnings and Precautions (5.13)].

Anaphylaxis

Inform patients that anaphylaxis has been reported with ingredients contained in DEMEROL Tablets and Oral Solution. Advise patients how to recognize such a reaction and when to seek medical attention [see Contraindications (4), Adverse Reactions (6)].

Pregnancy

Neonatal Opioid Withdrawal Syndrome

Inform female patients of reproductive potential that use of DEMEROL Tablets or Oral Solution for an extended period of time during pregnancy can result in neonatal opioid withdrawal syndrome, which may be life-threatening if not recognized and treated [see Warnings and Precautions (5.5), Use in Specific Populations (8.1)].

Embryo-Fetal Toxicity

Inform female patients of reproductive potential that DEMEROL Tablets and Oral Solution can cause fetal harm and to inform healthcare provider of a known or suspected pregnancy [see Use in Specific Populations (8.1)].

Lactation

Advise nursing mothers to monitor infants for increased sleepiness (more than usual), breathing difficulties, or limpness. Instruct nursing mothers to seek immediate medical care if they notice these signs [see Use in Specific Populations (8.2)].

Infertility

Inform patients that chronic use of opioids may cause reduced fertility. It is not known whether these effects on fertility are reversible [see Use in Specific Populations (8.3)].

Manufactured for and Distributed by:
Validus Pharmaceuticals LLC
Parsippany, NJ 07054
info@validuspharma.com
www.validuspharma.com
1-866-982-5438

© 2023 Validus Pharmaceuticals LLC

60037-15 December 2023

Medication Guide
DEMEROL® (de-meh-rol)
(meperidine hydrochloride, USP) Tablets and Oral Solution, CII

DEMEROL Tablets and Oral Solution are:

- A strong prescription pain medicine that contains an opioid (narcotic) that is used to manage the relief short-term (acute) pain, when other pain treatments such as non-opioid pain medicines do not treat your pain well enough or you cannot tolerate them.
- An opioid pain medicine that can put you at risk for overdose and death. Even if you take your dose correctly as prescribed you are at risk for opioid addiction, abuse, and misuse that can lead to death.

Important information about DEMEROL Tablets and Oral Solution:

- Get emergency help or call 911 right away if you take too much DEMEROL (overdose) Tablets or Oral Solution. When you first start taking DEMEROL Tablets or Oral Solution, when your dose is changed, or if you take too much (overdose), serious or life-threatening breathing problems that can lead to death may occur. Talk to your healthcare provider about naloxone, a medicine for the treatment of opioid overdose.
- Taking DEMEROL Tablets and Oral Solution with other opioid medicines, benzodiazepines, alcohol, or other central nervous system depressants (including street drugs) can cause severe drowsiness, decreased awareness, breathing problems, coma, and death.
- Never give anyone else your DEMEROL Tablets and Oral Solution. They could die from taking it. Selling or giving away DEMEROL Tablets and Oral Solution is against the law.
- Store DEMEROL Tablets and Oral Solution away from children and in a safe location not accessible by others, including visitors to the home.

Do not take DEMEROL Tablets and Oral Solution if you have:

- severe asthma, trouble breathing, or other lung problems.
- a bowel blockage or have narrowing of the stomach or intestines.
- allergy to meperidine

Before taking DEMEROL Tablets and Oral Solution, tell your healthcare provider if you have a history of:

- head injury, seizures

- liver, kidney, thyroid problems

- problems urinating

- pancreas or gallbladder problems

- abuse of street or prescription drugs, alcohol addiction, opioid overdose, or mental health problems.

Tell your healthcare provider if you are:

- notice your pain getting worse. If you pain gets worse after you take DEMEROL Tablets and Oral Solution, do not take more of DEMEROL Tablets and Oral Solution without first talking to your doctor. Talk to your doctor if the pain you have increases, if you feel more sensitive to pain, or if you have new pain after taking DEMEROL Tablets and Oral Solution.
- pregnant or planning to become pregnant. Use of DEMEROL Tablets and Oral Solution for an extended period of time during pregnancy can cause withdrawal symptoms in your newborn baby that could be life-threatening if not recognized and treated.
- breastfeeding. DEMEROL Tablets and Oral Solution passes into breast milk and may harm your baby. Carefully observe infants for increased sleepiness (more than usual), breathing difficulties, or limpness. Seek immediate medical care if you notice these signs.
- living in a household where there are small children or someone who has abused street or prescription drugs
- taking prescription or over-the-counter medicines, vitamins, or herbal supplements. Taking DEMEROL Tablets and Oral Solution with certain other medicines can cause serious side effects that could lead to death.

When taking DEMEROL Tablets and Oral Solution:

- Do not change your dose. Take DEMEROL Tablets and Oral Solution exactly as prescribed by your healthcare provider. Use the lowest dose possible for the shortest time needed.
- For acute (short-term) pain, you may only need to take DEMEROL Tablets or Oral Solution for a few days. You may have some DEMEROL Tablets or Oral Solution left over that you did not use. See disposal information at the bottom of this section for directions on how to safety throw away (dispose of) your unused DEMEROL Tablets and Oral Solution.
- Always use a calibrated measuring device for DEMEROL Oral Solution to correctly measure your dose. Never use a household teaspoon or tablespoon to measure DEMEROL Oral Solution.
- Mix each dose of DEMEROL oral solution into one-half glass of water before swallowing.
- Take your prescribed dose every 3 or 4 hours as necessary. Do not take more than your prescribed dose. If you miss a dose, take your next dose at your usual time.
- Call your healthcare provider if the dose you are taking does not control your pain.
- If you have been taking DEMEROL Tablets and Oral Solution regularly, do not stop taking DEMEROL Tablets and Oral Solution without talking to your healthcare provider.
- Dispose of expired, unwanted, or unused DEMEROL Tablets and Oral Solution by promptly flushing down the toilet, if a drug take-back option is not readily available. Visit www.fda.gov/drugdisposal for additional information on disposal of unused medicines.

While taking DEMEROL Tablets and Oral Solution DO NOT:

- Drive or operate heavy machinery, until you know how DEMEROL Tablets or Oral Solution affects you. DEMEROL Tablets or Oral Solution can make you sleepy, dizzy, or lightheaded.
- Drink alcohol or use prescription or over-the-counter medicines that contain alcohol. Using products containing alcohol during treatment with DEMEROL Tablets or Oral Solution may cause you to overdose and die.

The possible side effects of DEMEROL Tablets and Oral Solution:

- constipation, nausea, sleepiness, vomiting, tiredness, headache, dizziness, abdominal pain. Call your healthcare provider if you have any of these symptoms and they are severe.

Get emergency medical help or call 911 right away if you have:

- trouble breathing, shortness of breath, fast heartbeat, chest pain, swelling of your face, tongue, or throat, extreme drowsiness, light-headedness when changing positions, feeling faint, agitation, high body temperature, trouble walking, stiff muscles, or mental changes such as confusion.

These are not all the possible side effects of DEMEROL Tablets and Oral Solution. Call your healthcare provider for medical advice about side effects. You may report side effects to FDA at 1-800-FDA-1088 or www.fda.gov/medwatch.
For more information go to dailymed.nlm.nih.gov

Manufactured for and Distributed by: Validus Pharmaceuticals LLC, Parsippany, NJ, 07054
www.validuspharma.com or call 1-866-982-5438

This Medication Guide has been approved by the U.S. Food and Drug Administration. 60071-10 December 2023

PACKAGE LABEL

PRINCIPAL DISPLAY PANEL
NDC 30698-335-01
Demerol
(meperidine hydrochloride, USP) Tablets
50 mg
100 Tablets
Rx Only

PACKAGE LABEL

PRINCIPAL DISPLAY PANEL
NDC 30698-337-01
Demerol
(meperidine hydrochloride, USP) Tablets
100 mg
100 Tablets
Rx Only